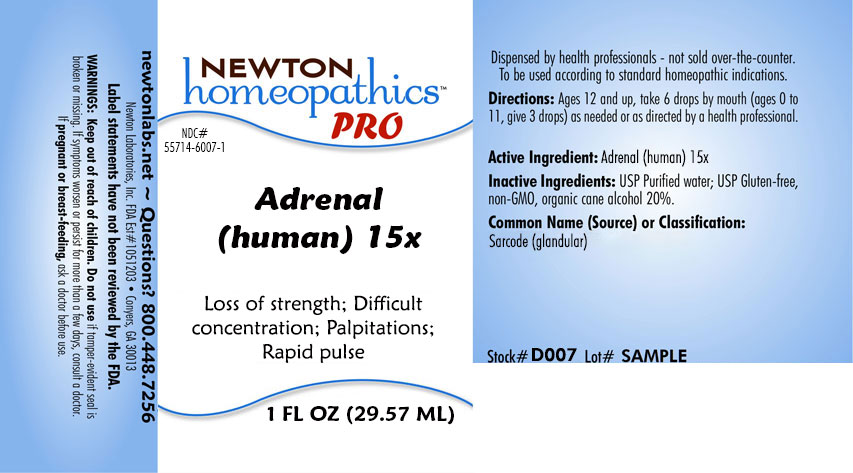 DRUG LABEL: Adrenal
NDC: 55714-6007 | Form: LIQUID
Manufacturer: Newton Laboratories, Inc.
Category: homeopathic | Type: HUMAN PRESCRIPTION DRUG LABEL
Date: 20201209

ACTIVE INGREDIENTS: HUMAN ADRENAL GLAND 15 [hp_X]/1 mL
INACTIVE INGREDIENTS: WATER; ALCOHOL

Adrenal 6007L

INDICATIONS & USAGE SECTION

Loss of strength; Difficult concentration; Palpitations; Rapid pulse.

DOSAGE & ADMINISTRATION SECTION

Directions: Ages 12 and up, take 6 drops by mouth (ages 0 to 11, give 3 drops) as needed or as directed by a health professional.

ACTIVE INGREDIENT SECTION

Adrenal gland (human)15x

PURPOSE SECTION

Loss of strength; Difficult concentration; Palpitations; Rapid pulse

INACTIVE INGREDIENT SECTION

Inactive Ingredients: USP Purified Water; USP Gluten-free, non-GMO, organic cane alcohol 20%.

QUESTIONS SECTION

newtonlabs.net - Questions? 1.800.448.7256

Newton Laboratories, Inc. FDA Est # 1051203 - Conyers, GA 30013

WARNINGS SECTION

Warning: Keep out of reach of children. Do not use if tamper - evident seal is broken or missing. Consult a doctor. If pregnant or breast-feeding, ask a doctor before use.

PREGNANCY SECTION

If pregnant or breast-feeding, ask a doctor before use.

OTC - KEEP OUT OF REACH OF CHILDREN SECTION

Keep out of reach of children.